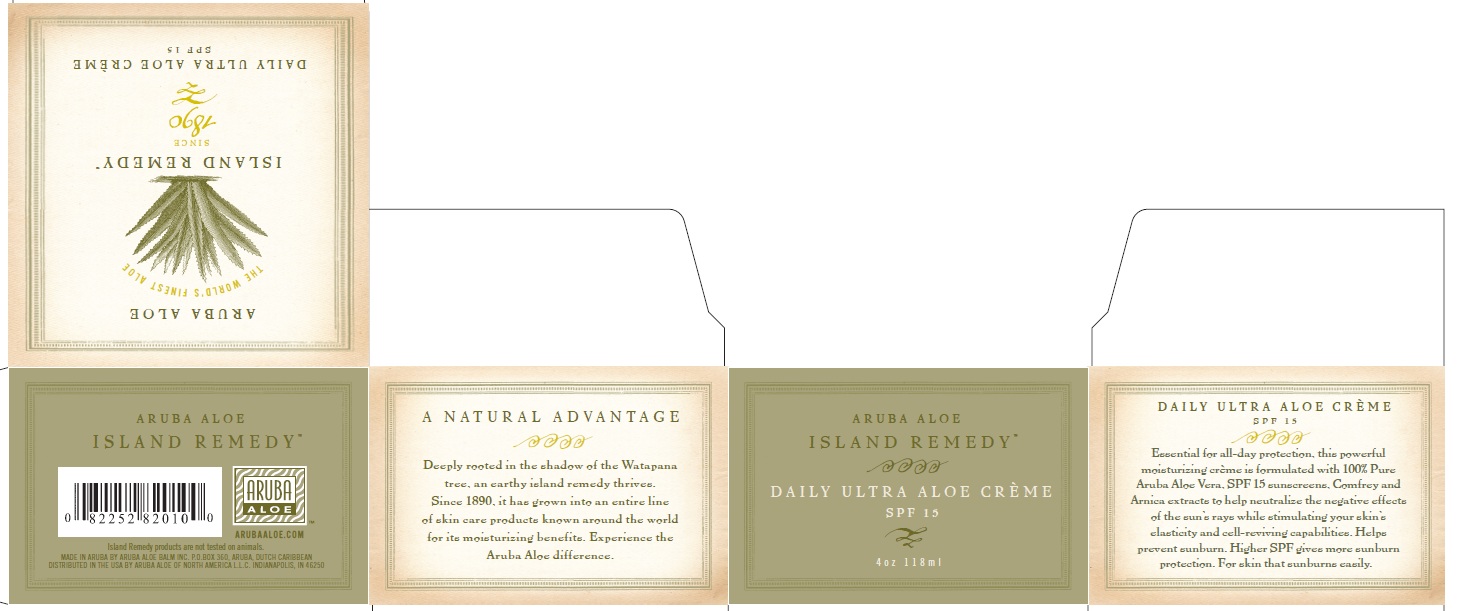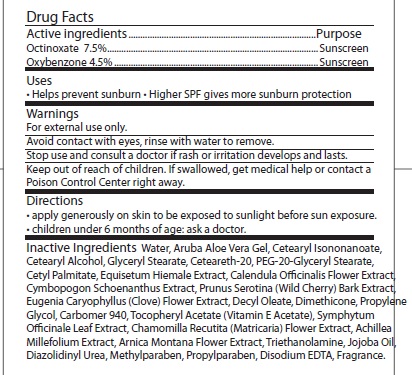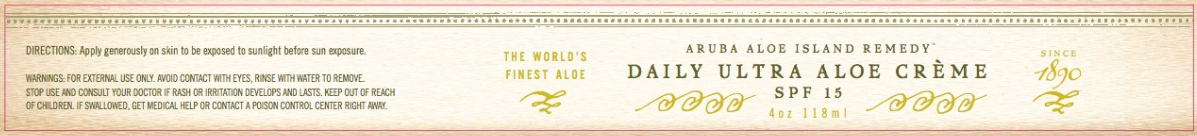 DRUG LABEL: ARUBA ALOE ISLAND REMEDY DAILY ULTRA ALOE
NDC: 53675-100 | Form: CREAM
Manufacturer: ARUBA ALOE BALM NV
Category: otc | Type: HUMAN OTC DRUG LABEL
Date: 20260204

ACTIVE INGREDIENTS: OCTINOXATE 75 mg/1 mL; OXYBENZONE 45 mg/1 mL
INACTIVE INGREDIENTS: WATER; ALOE VERA LEAF; CETEARYL ISONONANOATE; CETOSTEARYL ALCOHOL; GLYCERYL MONOSTEARATE; POLYOXYL 20 CETOSTEARYL ETHER; CETYL PALMITATE; EQUISETUM HYEMALE; CALENDULA OFFICINALIS FLOWER; PRUNUS SEROTINA BARK; CLOVE; DECYL OLEATE; DIMETHICONE; PROPYLENE GLYCOL; CARBOMER HOMOPOLYMER TYPE C; ALPHA-TOCOPHEROL ACETATE; MATRICARIA RECUTITA; ACHILLEA MILLEFOLIUM; ARNICA MONTANA FLOWER; TROLAMINE; JOJOBA OIL; DIAZOLIDINYL UREA; METHYLPARABEN; PROPYLPARABEN; EDETATE DISODIUM

ARUBA ALOE ISLAND REMEDY DAILY ULTRA ALOE CREME SPF 15

Drug Facts

Active Ingredients Purpose

Octinoxate 7.5% Sunscreen

Oxybenzone 4.5% Sunscreen

PURPOSE

Helps prevent sunburn

INDICATIONS AND USAGE

Higher SPF gives more sunburn protection.

Warnings

for external use only

Avoid contact with eyes, rince with water to remove.

Stop use and consult a doctor if rash or irritation develops and lasts.

KEEP OUT OF REACH OF CHILDREN

Keep out or reach of children. If swallowed, get medical help or contact a Poison Control Center right away.

Directions

apply generously on skin to be exposed to sunlight before sun exposure

children under 6 months of age: ask a doctor.

INACTIVE INGREDIENT

Inactive Ingredients: WATER, ARUBA ALOE VERA GEL, CETEARYL ISONONANOATE, CETEARYL ALCOHOL, GLYCERYL STEARATE, CETEARETH-20, PEG-20-GLYCERYL STEARATE, CETYL PALMITATE, EQUISETUM HIEMALE EXTRACT, CALENDULA OFFICINALIS FLOWER EXTRACT, CYMBOPOGON SCHOENANTHUS EXTRACT, PRUNUS SEROTINA (WILD CHERRY) BARK EXTRACT, EUGENIA CARYOPHYLLUS (CLOVE) FLOWER EXTRACT, DECYL OLEATE, DIMETHICONE, PROPYLENE GLYCOL, CARBOMER 940, TOCOPHERYL ACETATE (VITAMIN E ACETATE), SYMPHYTUM OFFICINALE LEAF EXTRACT, CHAMOMILLA RECUTITA (MATRICARIA) FLOWER EXTRACT, ACHILLEA MILLEFOLIUM EXTRACT, ARNICA MONTANA FLOWER EXTRACT, TRIETHANOLAMINE, JOJOBA OIL, DIAZOLIDINYL UREA, METHYLPARABEN, PROPYLPARABEN, DISODIUM EDTA, FRAGRANCE.

PACKAGE LABEL

ARUBA ALOE

ISLAND REMEDY

Island Remedy products are not tested on animals. MADE IN ARUBA BY ARUBA ALOE BALM INC PO BOX 360 ARUBA DUTCH CARIBBEAN

DISTRIBUTED IN THE USA BY ARUBA ALOE OF NORTH AMERICA L.L.C INDIANAPOLIS IN 46250

ARUBA ALOE

THE WORLDS FINEST ALOE

ISLAND REMEDY

SINCE 1890

DAILY ULTRA ALOE CREME SPF 15

A NATURAL ADVANTAGE
Deeply rooted in the shadow of the Watapana tree, an earthy island remedy thrives. Since 1890, it as grown into an entire line of skin care products known around the world for its moisturizing benefits. Experience the Aruba Aloe difference.

ARUBA ALOE ISLAND REMEDY

DAILY ULTRA ALOE CREME

SPF 15

4OZ 118 ML

DAILY ULTRA ALOE CREME

SPF 15

Essential for all-day protection, this powerful moisturizing creme is formulated with 10% Pure Aruba Aloe Vera, SPF 15 sunscreens. Comfrey and Arnica extracts to help neutralize the negative effects of the sun's rays while stimulating your skin's elasticity and cell-reviving capabilities. Helps prevent sunburn. Higher SPF gives more sunburn protection. for skin that sunburns easily.